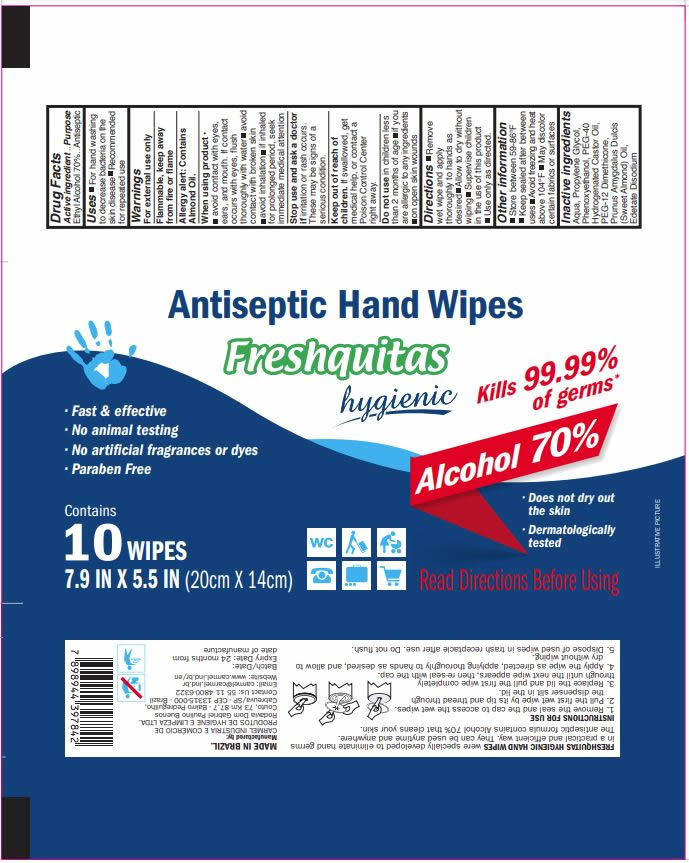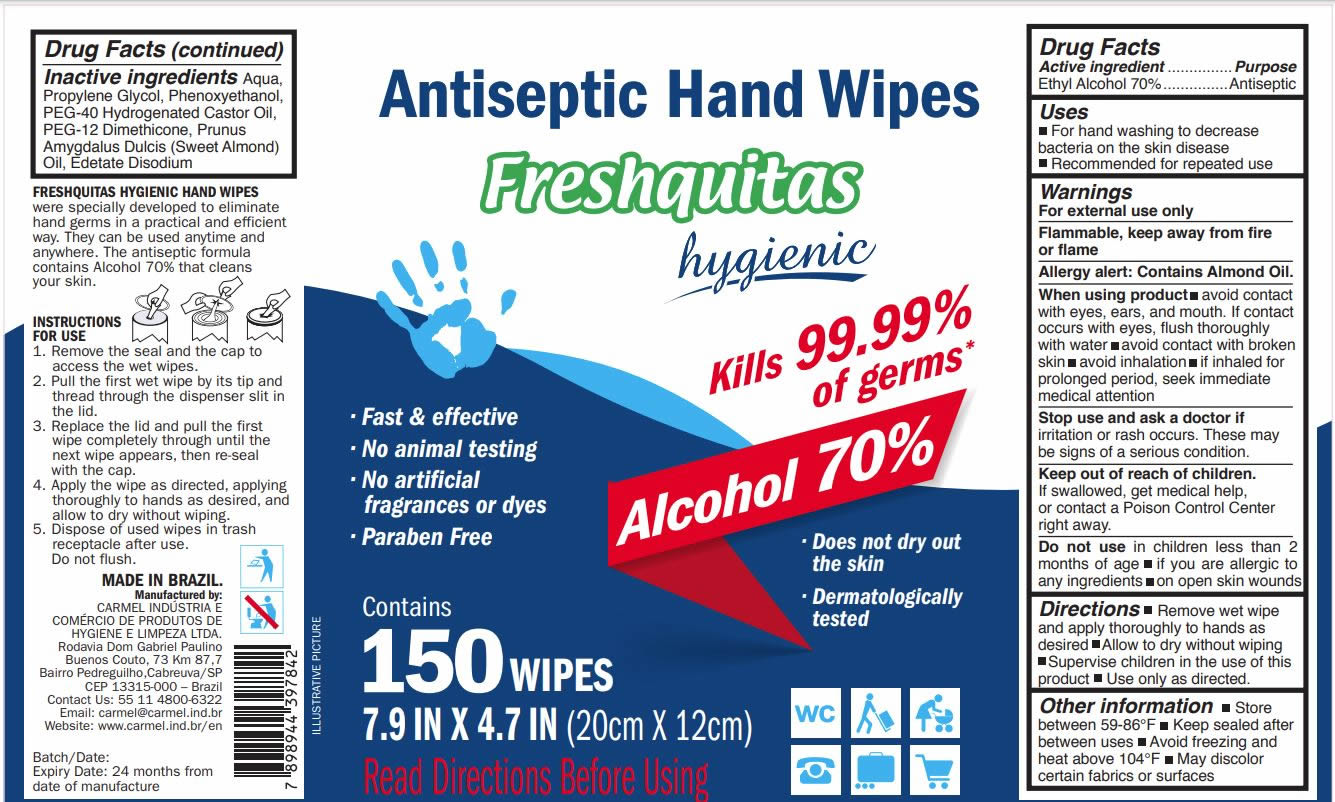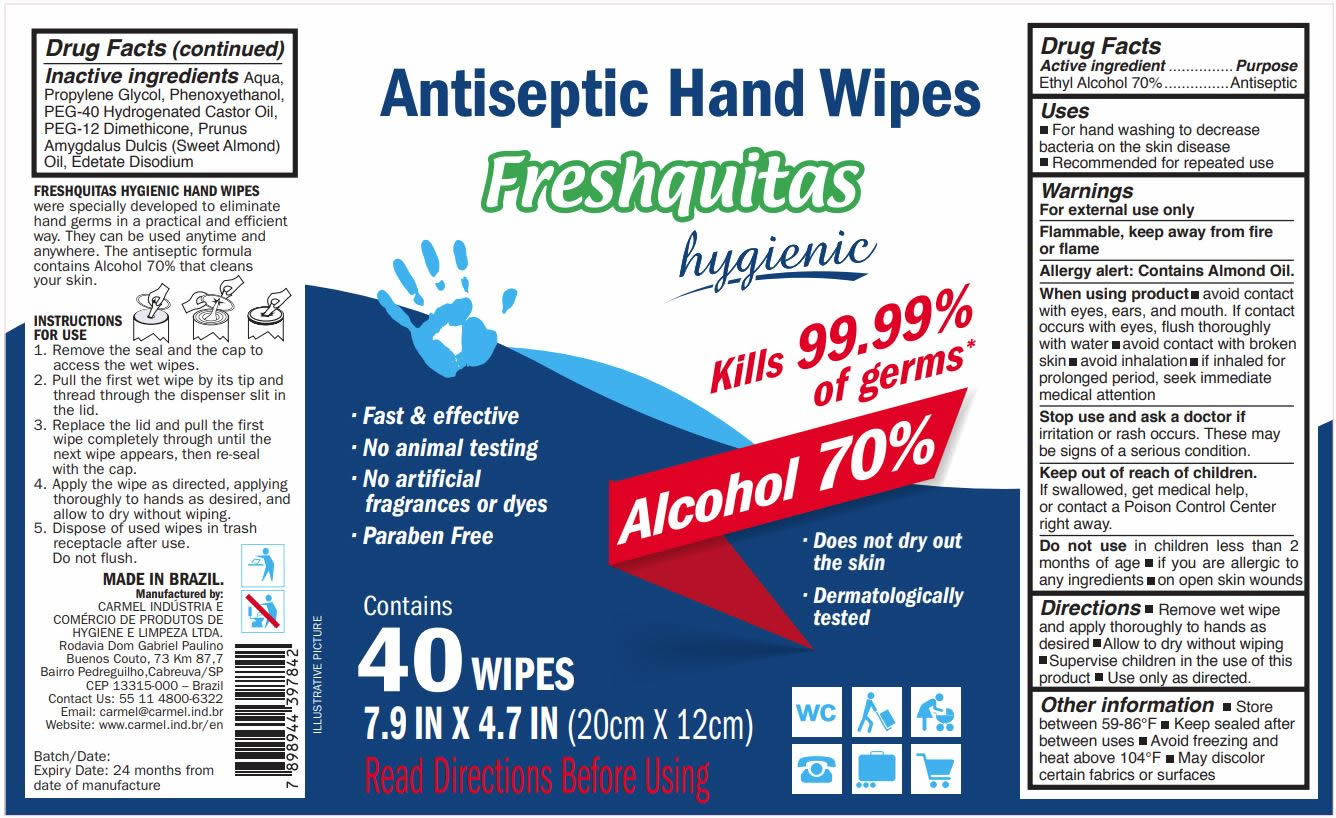 DRUG LABEL: Freshquitas Antiseptic Hand Wipes
NDC: 79089-501 | Form: CLOTH
Manufacturer: Carmel Industria e Comercio de Produtos de Higiene e Limpeza Ltda
Category: otc | Type: HUMAN OTC DRUG LABEL
Date: 20210211

ACTIVE INGREDIENTS: ALCOHOL 70 mL/100 mL
INACTIVE INGREDIENTS: EDETATE DISODIUM; PROPYLENE GLYCOL; PHENOXYETHANOL; WATER; POLYOXYL 40 HYDROGENATED CASTOR OIL; PEG-12 DIMETHICONE; ALMOND OIL

This is a package of hand sanitizer wipes containing the following ingredients:

1. Alcohol (ethanol) (70% volume/volume (v/v)).
2. Aqua
3. Propylene Glycol,
4. Phenoxyethanol, PEG-40
5. Hydrogenated Castor Oil
6. PEG-12 Dimethicone
7. Prunus Amygdalus Dulcis (Sweet Almond) Oil
8. Edetate Disodium

The firm does not add other active or inactive ingredients.

Active Ingredient(s)

Alcohol 70% v/v. Purpose: Antiseptic

Purpose

Antiseptic Hand Wipes

Use

- For hand washing to decrease bacteria on the skin disease
- Recommended for repeated use

Warnings

For external use only.

Flammable. Keep away from fire or flame.

Allergy Alert: Contains Almond Oil.

When using this product:

- avoid contact with eyes, ears, and mouth. If contact occurs with eyes, flush thoroughly with water
- avoid contact with broken skin
- avoid inhalation
- if inhaled for prolonged period, seek immediate medical attention

Stop use and ask a doctor if irritation or rash occurs. These may be signs of a serious condition.

Keep out of reach of children. If swallowed, get medical help or contact a Poison Control Center right away.

Do not use

- in children less than 2 months of age
- if you are allergic to any ingredients
- on open skin wounds

Directions

- Remove wet wipe and apply thoroughly to hands as desired
- Allow to dry without wiping
- Supervise children in the use of this product
- Use only as directed.

Other information

- Store between 59-86°F
- Keep sealed after between uses
- Avoid freezing and heat above 104°F
- May discolor certain fabrics or surfaces

Inactive ingredients

Aqua, Propylene Glycol, Phenoxyethanol, PEG-40 Hydrogenated Castor Oil, PEG-12 Dimethicone, Prunus Amygdalus Dulcis (Sweet Almond) Oil, Edetate Disodium

Package Label - Principal Display Panel

10 Wipes NDC: 79089-501-01

40 Wipes NDC: 79089-501-02

150 Wipes NDC: 79089-501-03